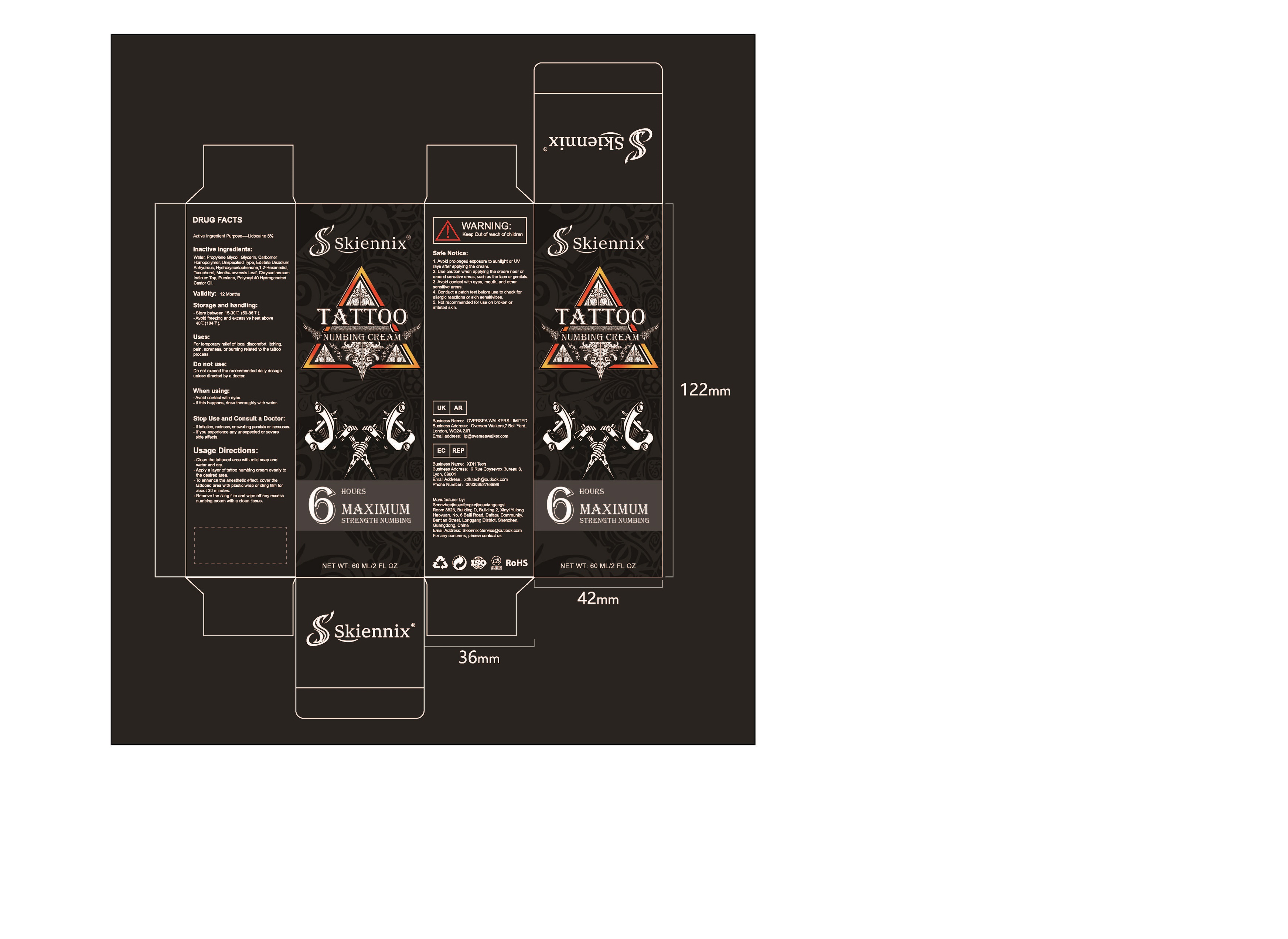 DRUG LABEL: TATTOO NUMBING
NDC: 84787-001 | Form: CREAM
Manufacturer: Shenzhen NuoYiyan Technology Co., Ltd.
Category: otc | Type: HUMAN OTC DRUG LABEL
Date: 20241008

ACTIVE INGREDIENTS: Lidocaine 5 g/100 mL
INACTIVE INGREDIENTS: WATER; PROPYLENE GLYCOL; GLYCERIN; CARBOMER HOMOPOLYMER, UNSPECIFIED TYPE; Edetate Disodium Anhydrous; HYDROXYACETOPHENONE; 1,2-HEXANEDIOL; TOCOPHEROL; MENTHA ARVENSIS LEAF; CHRYSANTHELLUM INDICUM TOP; PURSLANE; POLYOXYL 40 HYDROGENATED CASTOR OIL

Active Ingredient(s)

Lidocaine 5%

Purpose

local anesthetic

Use

For temporary relief of local discomfort, itching, pain,soreness or burning of the skin

Safe Notice

1. Avoid prolonged exposure to sunlight or UV rays after applying the cream.

2. Use caution when applying the cream near or around sensitive areas, such asthe face or genitals.

3. Avoid contact with eyes, mouth, and other sensitive areas.4. Not recommended for use on broken or irritated skin.

When using

1.Conduct a patch test before use to check for allergic reactions or skin sensitivities.
2.Avoid contact with eyes.
3.lf this happens, rinse thoroughly with water.

Stop Use and Consult a Doctor

If irritation, redness, or swelling persists or increases.
-lf you experience any unexpected or severe side effects.
- Do not exceed the recommended daily dosage unless directed by a doctor.

Keep out of reach of children.

USAGE DIRECTIONS

1. Clean the tattooed area with mild soap and water and dry.

2.Apply a layer of tattoo numbing cream evenly to the desired area.

3. To enhance the anesthetic effect, cover the tattooed area with plastic wrapor cling film for about 30 minutes.

4. Remove the cling film and wipe off any excess numbing cream with a cleantissue.

Storage and handling

Store between 15-30℃(59-86 F).
-Avoid freezing and excessive heat above 40℃(104 F).

Inactive ingredients

Water, Propylene Glycol, Glycerin, Carbomer Homopolymer, Unspecified Type,Edetate Disodium Anhydrous, Hydroxyacetophenone,1,2-Hexanediol, Tocopherol,Mentha arvensis Leaf, Chrysanthemum Indicum Top, Purslane, Polyoxyl 40Hydrogenated Castor Oil.